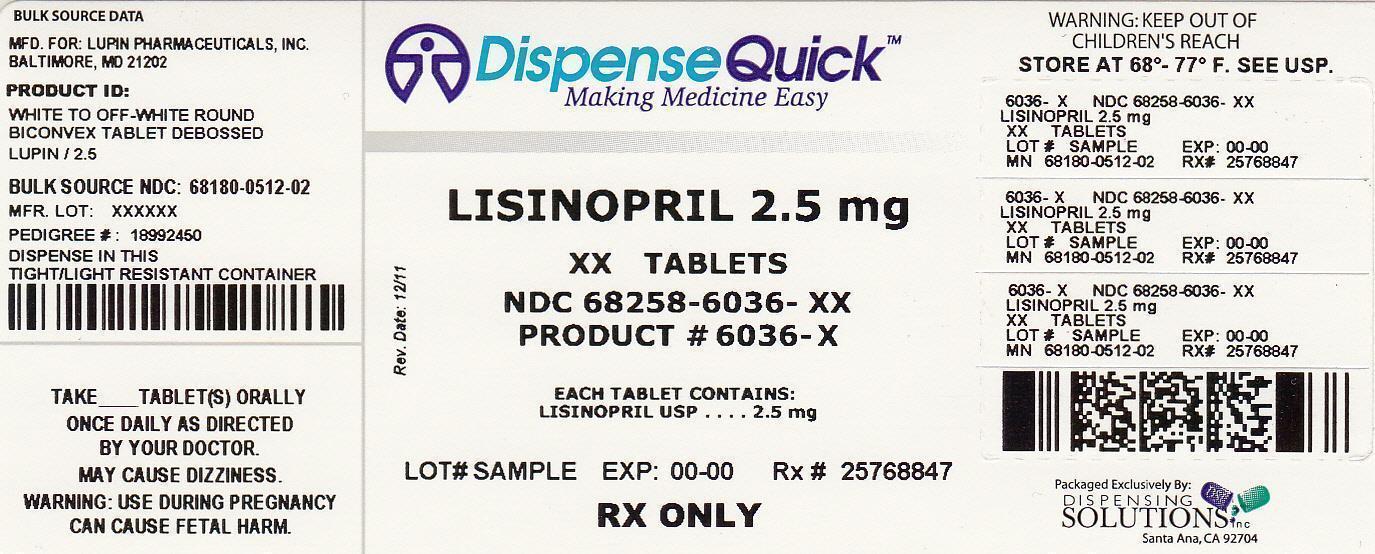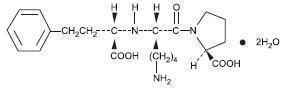 DRUG LABEL: Lisinopril
NDC: 68258-6036 | Form: TABLET
Manufacturer: Dispensing Solutions, Inc.
Category: prescription | Type: HUMAN PRESCRIPTION DRUG LABEL
Date: 20130716

ACTIVE INGREDIENTS: LISINOPRIL 2.5 mg/1 1
INACTIVE INGREDIENTS: ANHYDROUS DIBASIC CALCIUM PHOSPHATE; MANNITOL; COLLOIDAL SILICON DIOXIDE; STARCH, CORN; MAGNESIUM STEARATE

Lisinopril Tablets USP

2.5 mg, 5 mg, 10 mg, 20 mg, 30 mg and 40 mg

Rx only

BOXED WARNING

USE IN PREGNANCY

When used in pregnancy during the second and third trimesters, ACE inhibitors can cause injury and even death to the developing fetus. When pregnancy is detected, lisinopril should be discontinued as soon as possible. See WARNINGS, Fetal/Neonatal Morbidity and Mortality.

DESCRIPTION

Lisinopril is an oral long-acting angiotensin converting enzyme inhibitor. Lisinopril, a synthetic peptide derivative, is chemically described as (S)-1-[N2-(1-carboxy-3-phenylpropyl)-L-lysyl]-L-proline dihydrate. Its empirical formula is C21H31N3O5(2H2O and its structural formula is:

Lisinopril is a white to off-white, crystalline powder, with a molecular weight of 441.53. It is soluble in water and sparingly soluble in methanol and practically insoluble in ethanol.

Lisinopril tablets are supplied as 2.5 mg, 5 mg, 10 mg, 20 mg, 30 mg and 40 mg tablets for oral administration.

Inactive Ingredients:

2.5 mg tablets - colloidal silicon dioxide, dibasic calcium phosphate, magnesium stearate, mannitol, pre-gelatinized starch, starch.

5 mg, 10 mg, 20 mg and 30 mg tablets – colloidal silicon dioxide, dibasic calcium phosphate, magnesium stearate, mannitol, pre-gelatinized starch, red iron oxide, starch.

40 mg tablets - colloidal silicon dioxide, dibasic calcium phosphate, magnesium stearate, mannitol, pre-gelatinized starch, starch, yellow iron oxide.

CONTRAINDICATIONS

Lisinopril is contraindicated in patients who are hypersensitive to this product and in patients with a history of angioedema related to previous treatment with an angiotensin converting enzyme inhibitor and in patients with hereditary or idiopathic angioedema.

ADVERSE REACTIONS

Lisinopril has been found to be generally well tolerated in controlled clinical trials involving 1969 patients with hypertension or heart failure. For the most part, adverse experiences were mild and transient.

Hypertension

In clinical trials in patients with hypertension treated with lisinopril, discontinuation of therapy due to clinical adverse experiences occurred in 5.7% of patients. The overall frequency of adverse experiences could not be related to total daily dosage within the recommended therapeutic dosage range.

For adverse experiences occurring in greater than 1% of patients with hypertension treated with lisinopril or lisinopril plus hydrochlorothiazide in controlled clinical trials, and more frequently with lisinopril and/or lisinopril plus hydrochlorothiazide than placebo, comparative incidence data are listed in the table below:

PERCENT OF PATIENTS IN CONTROLLED STUDIES
 | Lisinopril (n=1349) Incidence (discontinuation) | Lisinopril/ Hydrochlorothiazide (n=629) Incidence (discontinuation) | Placebo (n=207) Incidence (discontinuation)
Body as a Whole
Fatigue | 2.5 (0.3) | 4.0 (0.5) | 1.0 (0.0)
Asthenia | 1.3 (0.5) | 2.1 (0.2) | 1.0 (0.0)
Orthostatic Effects | 1.2 (0.0) | 3.5 (0.2) | 1.0 (0.0)
Cardiovascular
Hypotension | 1.2 (0.5) | 1.6 (0.5) | 0.5 (0.5)
Digestive
Diarrhea | 2.7 (0.2) | 2.7 (0.3) | 2.4 (0.0)
Nausea | 2.0 (0.4) | 2.5 (0.2) | 2.4 (0.0)
Vomiting | 1.1 (0.2) | 1.4 (0.1) | 0.5 (0.0)
Dyspepsia | 0.9 (0.0) | 1.9 (0.0) | 0.0 (0.0)
Musculoskeletal
Muscle Cramps | 0.5 (0.0) | 2.9 (0.8) | 0.5 (0.0)
Nervous/Psychiatric
Headache | 5.7 (0.2) | 4.5 (0.5) | 1.9 (0.0)
Dizziness | 5.4 (0.4) | 9.2 (1.0) | 1.9 (0.0)
Paresthesia | 0.8 (0.1) | 2.1 (0.2) | 0.0 (0.0)
Decreased Libido | 0.4 (0.1) | 1.3 (0.1) | 0.0 (0.0)
Vertigo | 0.2 (0.1) | 1.1 (0.2) | 0.0 (0.0)
Respiratory
Cough | 3.5 (0.7) | 4.6 (0.8) | 1.0 (0.0)
Upper Respiratory Infection | 2.1 (0.1) | 2.7 (0.1) | 0.0 (0.0)
Common Cold | 1.1 (0.1) | 1.3 (0.1) | 0.0 (0.0)
Nasal Congestion | 0.4 (0.1) | 1.3 (0.1) | 0.0 (0.0)
Influenza | 0.3 (0.1) | 1.1 (0.1) | 0.0 (0.0)
Skin
Rash | 1.3 (0.4) | 1.6 (0.2) | 0.5 (0.5)
Urogenital
Impotence | 1.0 (0.4) | 1.6 (0.5) | 0.0 (0.0)

Chest pain and back pain were also seen, but were more common on placebo than lisinopril.

Heart Failure

In patients with heart failure treated with lisinopril for up to four years, discontinuation of therapy due to clinical adverse experiences occurred in 11% of patients. In controlled studies in patients with heart failure, therapy was discontinued in 8.1% of patients treated with lisinopril for 12 weeks, compared to 7.7% of patients treated with placebo for 12 weeks.
The following table lists those adverse experiences which occurred in greater than 1% of patients with heart failure treated with lisinopril or placebo for up to 12 weeks in controlled clinical trials, and more frequently on lisinopril than placebo.

 | Controlled Trials | Controlled Trials
 | Lisinopril (n=407) Incidence (discontinuation) 12 weeks | Placebo (n=155) Incidence (discontinuation) 12 weeks
Body as a Whole
Chest Pain | 3.4 (0.2) | 1.3 (0.0)
Abdominal Pain | 2.2 (0.7) | 1.9 (0.0)
Cardiovascular
Hypotension | 4.4 (1.7) | 0.6 (0.6)
Digestive
Diarrhea | 3.7 (0.5) | 1.9 (0.0)
Nervous/Psychiatric
Dizziness | 11.8 (1.2) | 4.5 (1.3)
Headache | 4.4 (0.2) | 3.9 (0.0)
Respiratory
Upper Respiratory Infection | 1.5 (0.0) | 1.3 (0.0)
Skin
Rash | 1.7 (0.5) | 0.6 (0.6)

Also observed at > 1% with lisinopril but more frequent or as frequent on placebo than lisinopril in controlled trials were asthenia, angina pectoris, nausea, dyspnea, cough, and pruritus.
Worsening of heart failure, anorexia, increased salivation, muscle cramps, back pain, myalgia, depression, chest sound abnormalities, and pulmonary edema were also seen in controlled clinical trials, but were more common on placebo than lisinopril.
In the two-dose ATLAS trial in heart failure patients, withdrawals due to adverse events were not different between the low and high groups, either in total number of discontinuation (17-18%) or in rare specific events (less than 1%). The following adverse events, mostly related to ACE inhibition, were reported more commonly in the high dose group:

% of patients Events | High Dose (N=1568) | Low Dose (N=1596)
Dizziness | 18.9 | 12.1
Hypotension | 10.8 | 6.7
Creatinine-increased | 9.9 | 7.0
Hyperkalemia | 6.4 | 3.5
NPN* increased | 9.2 | 6.5
Syncope | 7.0 | 5.1

*NPN = non-protein nitrogen

Acute Myocardial Infarction

In the GISSI-3 trial, in patients treated with lisinopril for six weeks following acute myocardial infarction, discontinuation of therapy occurred in 17.6% of patients.

Patients treated with lisinopril had a significantly higher incidence of hypotension and renal dysfunction compared with patients not taking lisinopril.

In the GISSI-3 trial, hypotension (9.7%), renal dysfunction (2%), cough (0.5%), post infarction angina (0.3%), skin rash and generalized edema (0.01%), and angioedema (0.01%) resulted in withdrawal of treatment. In elderly patients treated with lisinopril, discontinuation due to renal dysfunction was 4.2%.

Other clinical adverse experiences occurring in 0.3% to 1.0% of patients with hypertension or heart failure treated with lisinopril in controlled clinical trials and rarer, serious, possibly drug-related events reported in uncontrolled studies or marketing experience are listed below, and within each category are in order of decreasing severity:

Body as a Whole

Anaphylactoid reactions (see WARNINGS, Anaphylactoid and Possibly Related Reactions), syncope, orthostatic effects, chest discomfort, pain, pelvic pain, flank pain, edema, facial edema, virus infection, fever, chills, malaise.

Cardiovascular: Cardiac arrest; myocardial infarction or cerebrovascular accident possibly secondary to excessive hypotension in high risk patients (see WARNINGS, Hypotension); pulmonary embolism and infarction, arrhythmias (including ventricular tachycardia, atrial tachycardia, atrial fibrillation, bradycardia and premature ventricular contractions), palpitations, transient ischemic attacks, paroxysmal nocturnal dyspnea, orthostatic hypotension, decreased blood pressure, peripheral edema, vasculitis.

Digestive: Pancreatitis, hepatitis (hepatocellular or cholestatic jaundice) (see WARNINGS, Hepatic Failure), vomiting, gastritis, dyspepsia, heartburn, gastrointestinal cramps, constipation, flatulence, dry mouth.

Hematologic: Rare cases of bone marrow depression, hemolytic anemia, leukopenia/neutropenia and thrombocytopenia.

Endocrine: Diabetes mellitus, inappropriate antidiuretic hormone secretion.

Metabolic: Weight loss, dehydration, fluid overload, gout, weight gain. Cases of hypoglycemia in diabetic patients on oral antidiabetic agents or insulin have been reported in post-marketing experience (See PRECAUTIONS, Drug Interactions).

Musculoskeletal: Arthritis, arthralgia, neck pain, hip pain, low back pain, joint pain, leg pain, knee pain, shoulder pain, arm pain, lumbago.

Nervous System/Psychiatric: Stroke, ataxia, memory impairment, tremor, peripheral neuropathy (e.g., dysesthesia), spasm, paresthesia, confusion, insomnia, somnolence, hypersomnia, irritability, nervousness and mood alterations (including depressive symptoms).

Respiratory System: Malignant lung neoplasms, hemoptysis, pulmonary infiltrates, bronchospasm, asthma, pleural effusion, pneumonia, eosinophilic pneumonitis, bronchitis, wheezing, orthopnea, painful respiration, epistaxis, laryngitis, sinusitis, pharyngeal pain, pharyngitis, rhinitis, rhinorrhea.

Skin: Urticaria, alopecia, herpes zoster, photosensitivity, skin lesions, skin infections, pemphigus, erythema, flushing, diaphoresis, cutaneous pseudolymphoma. Other severe skin reactions have been reported rarely, including toxic epidermal necrolysis and Stevens-Johnson syndrome; causal relationship has not been established.

Special Senses: Visual loss, diplopia, blurred vision, tinnitus, photophobia, taste disturbances.

Urogenital System: Acute renal failure, oliguria, anuria, uremia, progressive azotemia, renal dysfunction (see PRECAUTIONS and DOSAGE AND ADMINISTRATION), pyelonephritis, dysuria, urinary tract infection, breast pain.

Miscellaneous: A symptom complex has been reported which may include a positive ANA, an elevated erythrocyte sedimentation rate, arthralgia/arthritis, myalgia, fever, vasculitis, eosinophilia and leukocytosis. Rash, photosensitivity or other dermatological manifestations may occur alone or in combination with these symptoms.

Angioedema: Angioedema has been reported in patients receiving lisinopril (0.1%) with an incidence higher in Black than in non-Black patients. Angioedema associated with laryngeal edema may be fatal. If angioedema of the face, extremities, lips, tongue, glottis and/or larynx occurs, treatment with lisinopril should be discontinued and appropriate therapy instituted immediately (See WARNINGS).

In rare cases, intestinal angioedema has been reported in post marketing experience.

Hypotension: In hypertensive patients, hypotension occurred in 1.2% and syncope occurred in 0.1% of patients with an incidence higher in Black than in non-Black patients. Hypotension or syncope was a cause of discontinuation of therapy in 0.5% of hypertensive patients. In patients with heart failure, hypotension occurred in 5.3% and syncope occurred in 1.8% of patients. These adverse experiences were possibly dose-related (see above data from ATLAS Trial) and caused discontinuation of therapy in 1.8% of these patients in the symptomatic trials. In patients treated with lisinopril for six weeks after acute myocardial infarction, hypotension (systolic blood pressure (100 mmHg) resulted in discontinuation of therapy in 9.7% of the patients. (See WARNINGS).

Fetal/Neonatal Morbidity and Mortality: See WARNINGS, Fetal/Neonatal Morbidity and Mortality.

Cough: See PRECAUTIONS, Cough

Pediatric Patients: No relevant differences between the adverse experience profile for pediatric patients and that previously reported for adult patients were identified.

CLINICAL LABORATORY TEST FINDINGS

Serum Electrolytes: Hyperkalemia (See PRECAUTIONS), hyponatremia.

Creatinine, Blood Urea Nitrogen: Minor increases in blood urea nitrogen and serum creatinine, reversible upon discontinuation of therapy, were observed in about 2% of patients with essential hypertension treated with lisinopril alone. Increases were more common in patients receiving concomitant diuretics and in patients with renal artery stenosis (See PRECAUTIONS). Reversible minor increases in blood urea nitrogen and serum creatinine were observed in approximately 11.6% of patients with heart failure on concomitant diuretic therapy. Frequently, these abnormalities resolved when the dosage of the diuretic was decreased.

Hemoglobin and Hematocrit: Small decreases in hemoglobin and hematocrit (mean decreases of approximately 0.4 g% and 1.3 vol%, respectively) occurred frequently in patients treated with lisinopril but were rarely of clinical importance in patients without some other cause of anemia. In clinical trials, less than 0.1% of patients discontinued therapy due to anemia. Hemolytic anemia has been reported; a causal relationship to lisinopril cannot be excluded.

Liver Function Tests: Rarely, elevations of liver enzymes and/or serum bilirubin have occurred (See WARNINGS, Hepatic Failure).

In hypertensive patients, 2.0% discontinued therapy due to laboratory adverse experiences, principally elevations in blood urea nitrogen (0.6%), serum creatinine (0.5%) and serum potassium (0.4%).

In the heart failure trials, 3.4% of patients discontinued therapy due to laboratory adverse experiences; 1.8% due to elevations in blood urea nitrogen and/or creatinine and 0.6% due to elevations in serum potassium.

In the myocardial infarction trial, 2.0% of patients receiving lisinopril discontinued therapy due to renal dysfunction (increasing creatinine concentration to over 3 mg/dL or a doubling or more of the baseline serum creatinine concentration); less than 1.0% of patients discontinued therapy due to other laboratory adverse experiences: 0.1% with hyperkalemia and less than 0.1% with hepatic enzyme alterations.

OVERDOSAGE

Following a single oral dose of 20 g/kg no lethality occurred in rats, and death occurred in one of 20 mice receiving the same dose. The most likely manifestation of overdosage would be hypotension, for which the usual treatment would be intravenous infusion of normal saline solution.

Lisinopril can be removed by hemodialysis (See WARNINGS, Anaphylactoid Reactions During Membrane Exposure).

HOW SUPPLIED

Lisinopril Tablets, USP are available as:

2.5 mg tablet is a white to off-white, round, biconvex uncoated tablet with ‘LUPIN" debossed on one side and "2.5" on other side. They are available as follows:

Bottles of 90 NDC 68180-512-09

Bottles of 100 NDC 68180-512-01

Bottles of 500 NDC 68180-512-02

Bottles of 1000 NDC 68180-512-03

5 mg tablet is a pink coloured, round, biconvex uncoated tablet with "5" debossed on one side and breakline on other side. They are available as follows:

Bottles of 90 NDC 68180-513-09

Bottles of 100 NDC 68180-513-01

Bottles of 500 NDC 68180-513-02

Bottles of 1000 NDC 68180-513-03

Bottles of 5000 NDC 68180-513-05

10 mg tablet is a pink coloured, round, biconvex uncoated tablet with "LUPIN" debossed on one side and "10" on other side. They are available as follows:

Bottles of 90 NDC 68180-514-09

Bottles of 100 NDC 68180-514-01

Bottles of 500 NDC 68180-514-02

Bottles of 1000 NDC 68180-514-03

Bottles of 5000 NDC 68180-514-05

20 mg tablet is a pink coloured, round, biconvex uncoated tablet with "LUPIN" debossed on one side and "20" on other side. They are available as follows:

Bottles of 90 NDC 68180-515-09

Bottles of 100 NDC 68180-515-01

Bottles of 500 NDC 68180-515-02

Bottles of 1000 NDC 68180-515-03

Bottles of 5000 NDC 68180-515-05

30 mg tablet is a red coloured, round, biconvex uncoated tablet with "LUPIN" debossed on one side and "30" on other side. They are available as follows:

Bottles of 90 NDC 68180-516-09

Bottles of 100 NDC 68180-516-01

Bottles of 500 NDC 68180-516-02

Bottles of 1000 NDC 68180-516-03

40 mg tablet is a yellow coloured, round, biconvex uncoated tablet with "LUPIN" debossed on one side and "40" on other side. They are available as follows:

Bottles of 90 NDC 68180-517-09

Bottles of 100 NDC 68180-517-01

Bottles of 500 NDC 68180-517-02

Bottles of 1000 NDC 68180-517-03

Bottles of 2000 NDC 68180-517-04

Storage:

Store at 20º to 25ºC (68º to 77ºF)[see USP Controlled Room Temperature]. Protect from moisture, freezing and excessive heat. Dispense in a tight container.

Manufactured for:

Lupin Pharmaceuticals, Inc.

Baltimore, Maryland 21202

United States.

Manufactured by:

Lupin Limited

Goa 403 722

INDIA.

Or

Lupin Limited

Pithampur (M.P.) 454 775

INDIA.

PRINCIPAL DISPLAY PANEL

NDC 68258-6036-XX
NDC 68258-6036-03

NDC 68258-6036-09